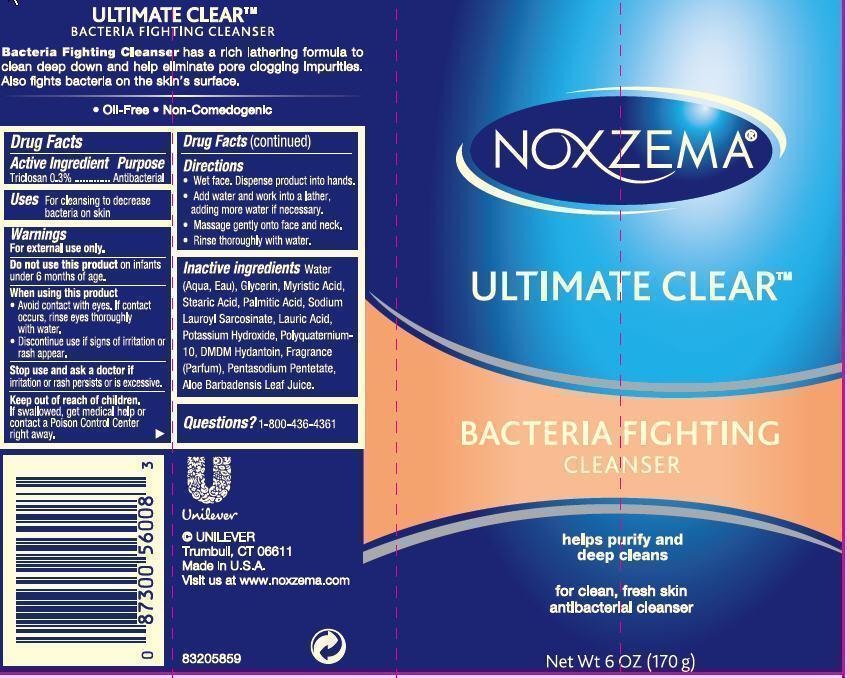 DRUG LABEL: Noxzema 
NDC: 64942-1264 | Form: SOAP
Manufacturer: CONOPCO Inc. d/b/a Unilever
Category: otc | Type: HUMAN OTC DRUG LABEL
Date: 20121002

ACTIVE INGREDIENTS: Triclosan 0.003 g/1 g
INACTIVE INGREDIENTS: Water; Aloe Vera Leaf; Glycerin; Iodopropynyl Butylcarbamate; Palmitic Acid; Myristic Acid; Stearic Acid; Lauric Acid; Potassium Hydroxide

NOXZEMA®

Drug Facts

Active ingredient

Triclosan 0.3%

Purpose

Antibacterial

Uses

For cleansing to decrease bacteria on skin

Warnings

DO NOT USE

- For external use only. Do not use on infants under 6 months of age.

When using this product

- Avoid contact with eyes. If contact occurs, rinse eyes thoroughly with water.
- Discontinue use if signs of irritation or rash appear.

Stop use and ask a doctor if irritation or rash persists or is excessive.

Keep out of reach of children. If swallowed, get medical help or contact a Poison Control Center right away.

Directions

- Wet face. Dispense product into hands.
- Add water and work into a lather, adding more water if necessary.
- Massage gently onto face and neck.
- Rinse thoroughly with water.

Inactive ingredients

Water (Aqua, Eau), Glycerin, Myristic Acid, Stearic Acid, Palmitic Acid, Sodium Lauroyl Sarcosinate, Lauric Acid, Potassium Hydroxide, Polyquaternium-10, DMDM Hydantoin, Fragrance (Parfum), Pentasodium Pentetate, Aloe Barbadensis Leaf Juice.

Questions?

1-800-436-4361